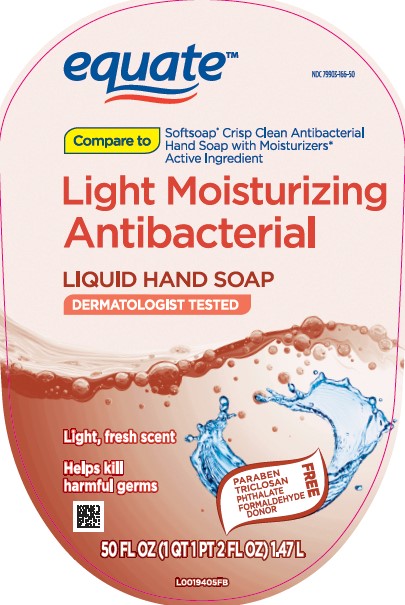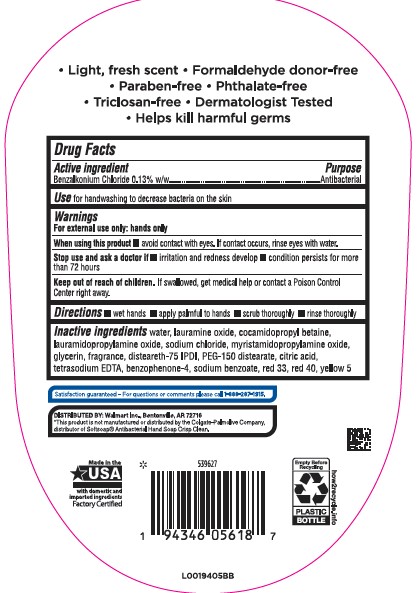 DRUG LABEL: Moisturizing Antibacterial
NDC: 79903-166 | Form: SOAP
Manufacturer: Walmart Inc.
Category: otc | Type: HUMAN OTC DRUG LABEL
Date: 20260227

ACTIVE INGREDIENTS: BENZALKONIUM CHLORIDE 1.3 mg/1 mL
INACTIVE INGREDIENTS: WATER; LAURAMINE OXIDE; COCAMIDOPROPYL BETAINE; LAURAMIDOPROPYLAMINE OXIDE; SODIUM CHLORIDE; MYRISTAMIDOPROPYLAMINE OXIDE; GLYCERIN; DISTEARETH-75 ISOPHORONE DIISOCYANATE; PEG-150 DISTEARATE; CITRIC ACID MONOHYDRATE; EDETATE SODIUM; SULISOBENZONE; SODIUM BENZOATE; D&C RED NO. 33; FD&C RED NO. 40; FD&C YELLOW NO. 5

Equate 279.003/279AD-AE
Light Moisturizing Antibacterial Hand Soap

Claims

- Light, fresh Scent
- Formaldehyde donor-free
- Paraben-free
- Phthalate-Free
- Triclosan-free
- Dermatologist Tested
- Helps kill harmful germs

Active ingredient

Benzalkonium chlroide 0.13%

Purpose

Antibacterial

Use

for handwashing to decrease bacteria on the skin

Warnings

For external use only: hands only

When using this product

avoid contact with eyes. If contact occurs, rinse eyes thoroughly with water.

Stop use and ask a doctor if

- irritation and redness develop
- condition persists for more than 72 hours

Keep out of reach of children.

If swallowed, get medical help or contact a Poison Control Center right away.

Directions

- wet hands
- apply palmful to hands
- scrub thoroughly
- rinse thoroughly

Inactive ingredients

water, lauramine oxide, cocamidopropyl betaine, lauramidopropylamine oxide, sodium chloride, myristamidopropylamine oxide, glycerin, fragrance, disteareth-75 IPDI, PEG-150 distearate, citric acid, tetrasodium EDTA, benzophenone-4, sodium benzoate, red 33, red 40, yellow 5

ADVERSE REACTION

Satsfaction Guaranteed - for questions or comments please call 1-888-287-1915.

Distributed by: Walmart Inc., Bentonville, AR 72716

Made in the U.S.A. with domestic and imported ingredients

Factory Certified

how2recycle.info

Empty Before Recycling

Plastic Bottle

Disclaimer

*This product is not manufactured or distributed by Colgate-Palmolive Company, distributor of SoftsoapAntibacterial Hand Soap Crisp Clean.

principal display panel

Equate™

NDC 79903-166-50

Compare to Softsoap®Crisp Clean Antibacterial Hand Soap with Moisturizers* Active Ingredient

Light Moisturizing Antibacterial

Liquid Hand Soap

Dermatologist Tested

Light, fresh scent

Helps kill harmful germs

Paraben - Triclosan - Phthalate - Formaledehyde Donor FREE

50 FL OZ (1 QT 1 PT 2 FL OZ) 1.47 L